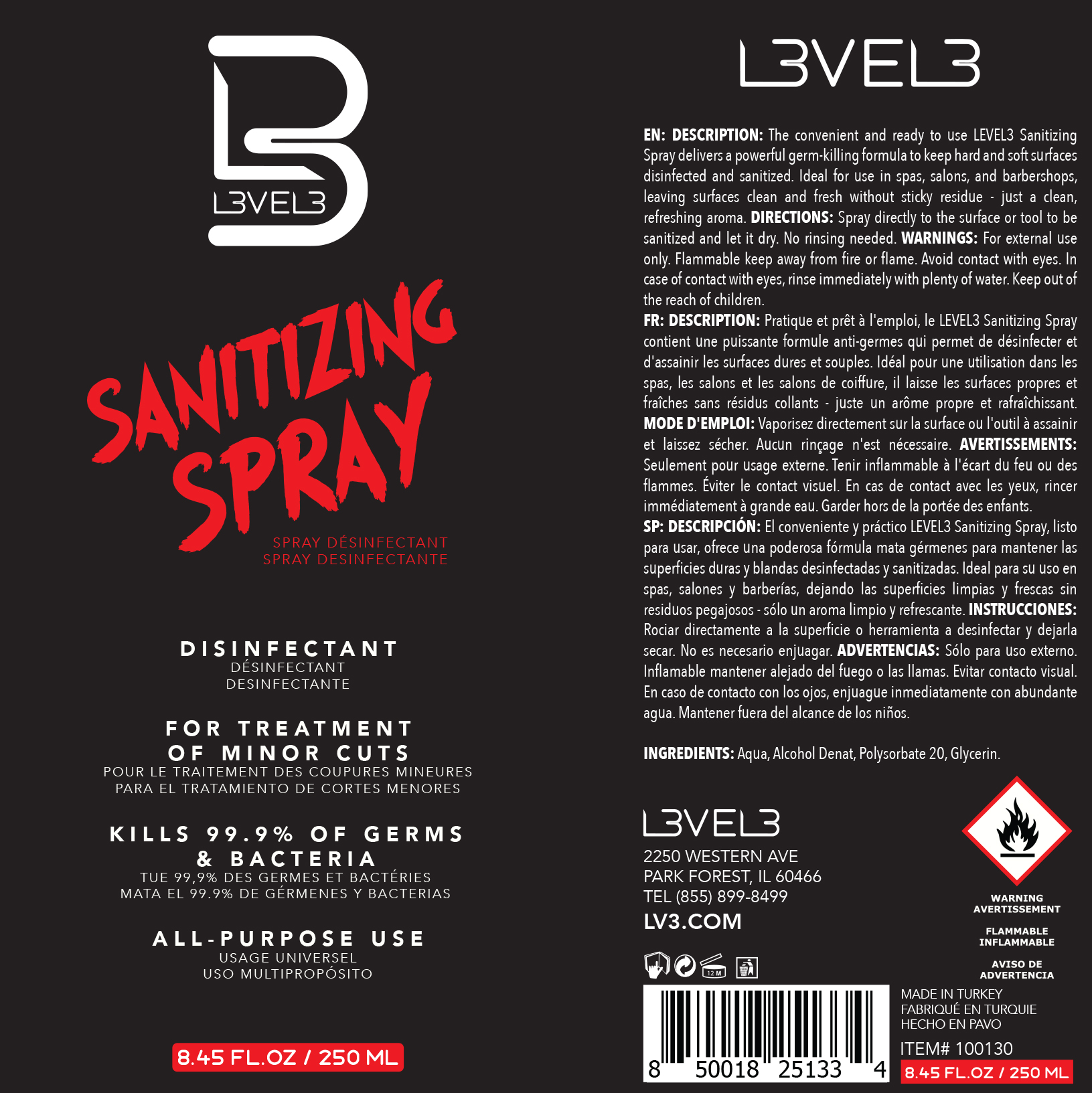 DRUG LABEL: Sanitizing
NDC: 80848-002 | Form: SPRAY
Manufacturer: L3VEL3 LLC
Category: otc | Type: HUMAN OTC DRUG LABEL
Date: 20201015

ACTIVE INGREDIENTS: ALCOHOL 70 mL/100 mL
INACTIVE INGREDIENTS: GLYCERIN 1 mL/100 mL; POLYSORBATE 20 1 mL/100 mL; WATER

Sanitizing Spray

Purpose

Sanitizing Spray

Description:

The convenient and ready to use LEVEL3 Spray Sanitizer delivers a powerful germ-killing formula to keep hard and soft surfaces disinfected and sanitized. Ideal for use in spas, salons, and barbershops, leaving surfaces clean and fresh without sticky residue - just a clean, refreshing aroma.

Directions

Spray directly to the surface or tool to be sanitized and let it dry. No rinsing needed.

Warnings

For external use only. Flammable keep away from fire or flame. Avoid contact with the eyes. In case of contact with eyes, rinse with plenty of water. Keep out of the reach of children.

Keep out of reach of children.

Active Ingredient(s)

Alcohol Denat

Inactive ingredients

Aqua, Glycerin, Polysorbate 20.

Package Label - Principal Display Panel

Sanitizing Spray 250 mL Label NDC: 80848-002-01